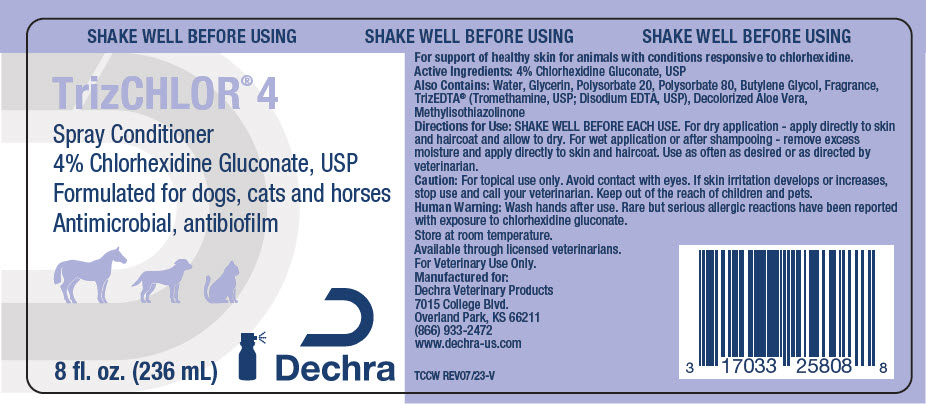 DRUG LABEL: TrizChlor 4 Conditioner
NDC: 17033-258 | Form: SOLUTION
Manufacturer: Dechra Veterinary Products
Category: animal | Type: OTC ANIMAL DRUG LABEL
Date: 20240226

ACTIVE INGREDIENTS: Chlorhexidine Gluconate 40 mg/1 mL

TrizChlor® 4 Spray Conditioner

VETERINARY INDICATIONS

For support of healthy skin for animals with conditions responsive to chlorhexidine.

DESCRIPTION

Active Ingredients: 4% Chlorhexidine Gluconate, USP

Also Contains: Water, Glycerin, Polysorbate 20, Polysorbate 80, Butylene Glycol, Fragrance, TrizEDTA® (Tromethamine, USP; Disodium EDTA, USP), Decolorized Aloe Vera, Methylisothiazolinone

DOSAGE AND ADMINISTRATION

Directions for Use: SHAKE WELL BEFORE EACH USE. For dry application - apply directly to skin and haircoat and allow to dry. For wet application or after shampooing - remove excess moisture and apply directly to skin and haircoat. Use as often as desired or as directed by veterinarian.

SAFE HANDLING WARNING

Caution: For topical use only. Avoid contact with eyes. If skin irritation develops or increases, stop use and call your veterinarian. Keep out of the reach of children and pets.

Human Warning: Wash hands after use. Rare but serious allergic reactions have been reported with exposure to chlorhexidine gluconate.

STORAGE AND HANDLING

Store at room temperature.

Available through licensed veterinarians.

For Veterinary Use Only.

Manufactured for:
Dechra Veterinary Products
7015 College Blvd.
Overland Park, KS 66211
(866) 933-2472
www.dechra-us.com

TCCW REV07/23-V

PRINCIPAL DISPLAY PANEL - 236 mL Bottle Label

SHAKE WELL BEFORE USING

TrizCHLOR® 4

Spray Conditioner
4% Chlorhexidine Gluconate, USP
Formulated for dogs, cats and horses
Antimicrobial, antibiofilm

8 fl. oz. (236 mL)

Dechra